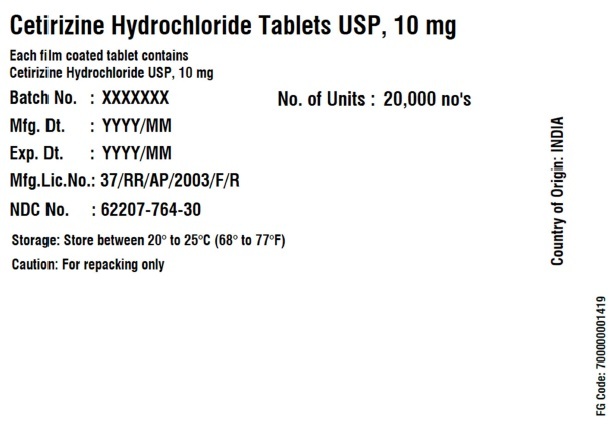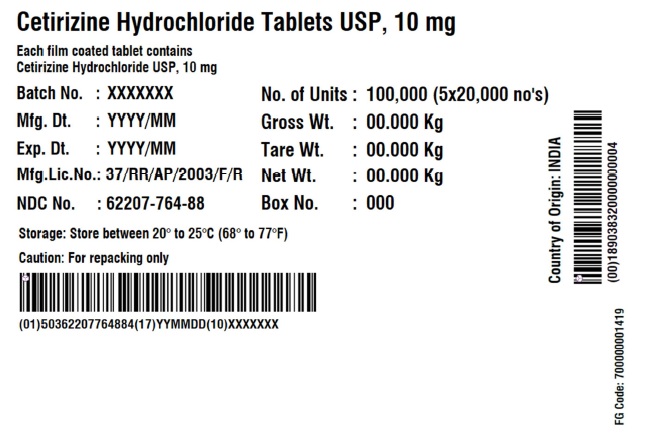 DRUG LABEL: Cetirizine hydrochloride
NDC: 62207-764 | Form: TABLET, COATED
Manufacturer: Granules India Ltd
Category: otc | Type: HUMAN OTC DRUG LABEL
Date: 20250805

ACTIVE INGREDIENTS: CETIRIZINE HYDROCHLORIDE 10 mg/1 1
INACTIVE INGREDIENTS: LACTOSE MONOHYDRATE; CROSCARMELLOSE SODIUM; SILICON DIOXIDE; MAGNESIUM STEARATE; CELLULOSE, MICROCRYSTALLINE; HYPROMELLOSE, UNSPECIFIED; TITANIUM DIOXIDE; POLYETHYLENE GLYCOL

Cetrizine Hydrochloride Tablets